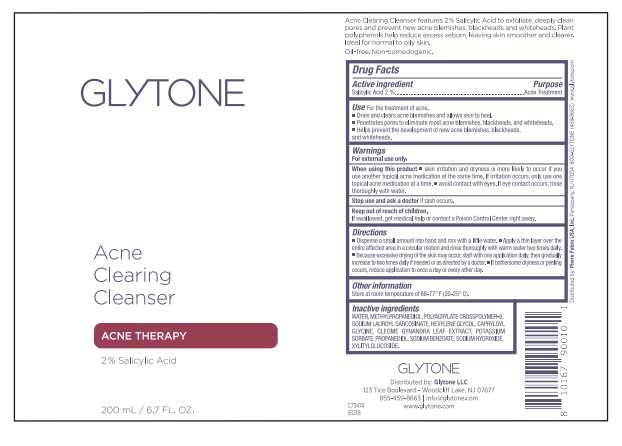 DRUG LABEL: Acne Clearing Cleanser
NDC: 84262-010 | Form: GEL
Manufacturer: GLYTONE LLC
Category: otc | Type: HUMAN OTC DRUG LABEL
Date: 20240628

ACTIVE INGREDIENTS: SALICYLIC ACID 2 g/2 mL
INACTIVE INGREDIENTS: LAURIC ACID; SODIUM LAUROYL SARCOSINATE; POTASSIUM SORBATE; WATER; SODIUM BENZOATE; METHYLPROPANEDIOL; SODIUM CHLORIDE; PROPANEDIOL; CLEOME GYNANDRA LEAF; TERT-BUTYL ALCOHOL; HEXYLENE GLYCOL; CAPRYLOYL GLYCINE; SODIUM HYDROXIDE; XYLITYLGLUCOSIDE; EDETATE SODIUM; AMMONIUM ACRYLOYLDIMETHYLTAURATE, DIMETHYLACRYLAMIDE, LAURYL METHACRYLATE AND LAURETH-4 METHACRYLATE COPOLYMER, TRIMETHYLOLPROPANE TRIACRYLATE CROSSLINKED (45000 MPA.S)

Glytone Acne Clearing Cleanser

Active Ingredient

Salicylic Acid 2%

Purpose

Acne Treatment

Use

For the treatment of acne.

- Dries and clears acne blemishes and allows skin to heal.
- Penetrates pores to eliminate most acne blemishes, blackheads, and whiteheads.
- Helps prevent the development of new acne blemishes, blackheads, and whiteheads.

Warnings

For external use only.

When using this product

- skin irritation and dryness is more likely to occur if you use another topical acne medication at the same time. If irritation occurs, only use one topical acne medication at a time.
- avoid contact with eyes. If eye contact occurs, rinse thoroughly with water.

Stop use and ask a doctor

if rash occurs.

Keep ou tof reach of children.

If swallowed, get medical help or contact a Poison Control Center right away.

Directions

- Dispense a small amount into hand and mix with a little water.
- Apply a thin layer over the entire affected area in a circular motion and rinse thoroughly with warm water two times daily.
- Because excessive dry of the skin may occur, start with one application daily, then gradually increase to two times daily if needed or as directed by a doctor.
- If bothersome dryness or peeling occurs, reduce application to once a day or every other day.

Other Information

Store at room temperature of 68-77F (20-25C).

Inactive Ingredients

WATER, METHYLPROPANEDIOL, POLYACRYLATE CROSSPOLYMER-6, SODIUM LAUROYL SARCOSINATE, HEXYLENE GLYCOL, CAPRYLOYL GLYCINE, CLEOME GYNANDRA LEAF EXTRACT, POTASSIUM SORBATE, PROPANEDIOL, SODIUM BENZOATE, SODIUM HYDROXIDE, XYLITYLGLUCOSIDE

PRINCIPAL DISPLAY PANEL

GLYTONE

ACNE CLEARING CLEANSER

ACNE THERAPY

2% SALICYLIC ACID

200 ML / 6.7 FL. OZ